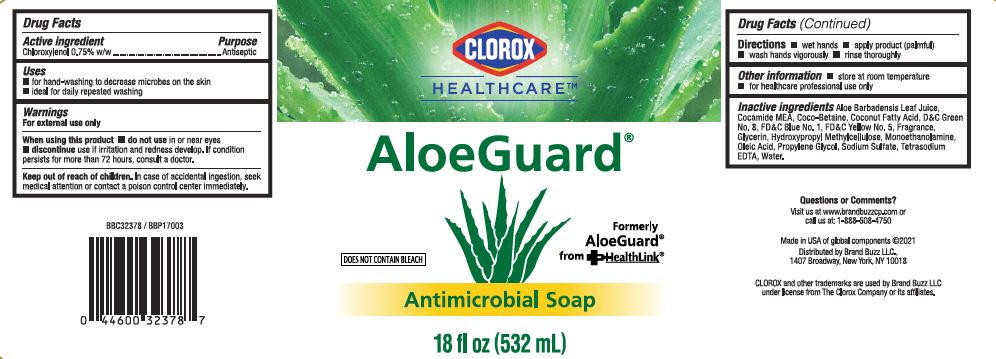 DRUG LABEL: Clorox HealthCare AloeGuard Antimicrobial
NDC: 26509-0201 | Form: LIQUID
Manufacturer: The Clorox Company
Category: otc | Type: HUMAN OTC DRUG LABEL
Date: 20210421

ACTIVE INGREDIENTS: CHLOROXYLENOL 7.5 mg/1 mL
INACTIVE INGREDIENTS: COCO-BETAINE; D&C GREEN NO. 8; OLEIC ACID; PROPYLENE GLYCOL; SODIUM SULFATE; ALOE VERA LEAF; FD&C BLUE NO. 1; FD&C YELLOW NO. 5; GLYCERIN; EDETATE SODIUM; WATER; COCONUT ACID; HYPROMELLOSE, UNSPECIFIED; MONOETHANOLAMINE; COCO MONOETHANOLAMIDE

Clorox HealthCare AloeGuard Antimicrobial Soap NDC 26509-0201

Active ingredient

Chloroxylenol 0.75% w/w

Purpose

Antiseptic

Uses

- for hand-washing to decrease microbes on the skin
- ideal for daily repeated washings

Warnings

For external use only

When using this product

- do not use in or near eyes
- discontue use if irritation and redness develop. If condition persists for more than 72 hours, consult a doctor.

Keep out of reach of children.

In case of accidental ingestion, seek medical attention or contact a poison control center immediately.

Directions

- wet hands
- apply product (palmful)
- wash hands vigorously
- rinse thoroughly

Other information

- store at room temperatuure
- for healthcare professional use only

Inactive ingredients

Aloe Barbadensis Leaf Juice, Cocamide MEA, Coco-Betaine, Coconut Fatty Acid, D&C Green No. 8, FD&C Blue No. 1, FD&C Yellow No. 5, Fragrance, Glycerin, Hydroxypropyl Methylcellulose, Monoethanolamine, Oleic Acid, Propylene Glycol Sodium Sulfate, Tetrasodium EDTA, Water.

PACKAGE LABEL

CLOROX

HEALTHCARE

AloeGuard

DOES NOT CONTAIN BLEACH

Formerly

AloeGuard

from Healthlink

Antimicrobial Soap

18 fl oz (532 mL)